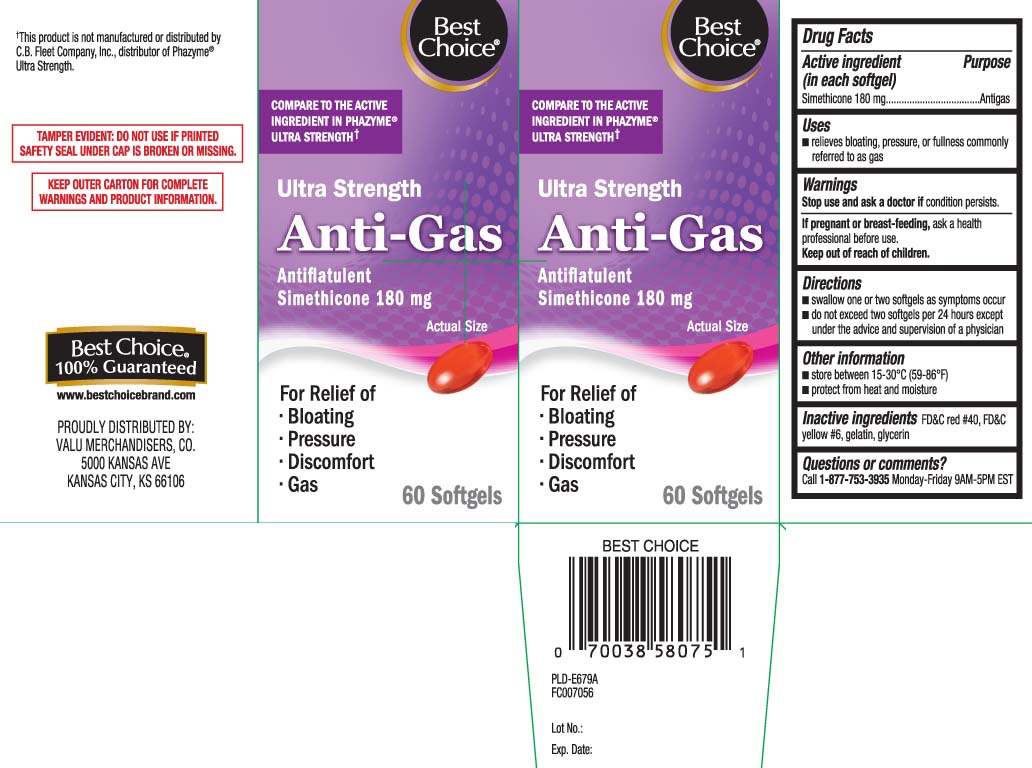 DRUG LABEL: Anti-Gas
NDC: 63941-773 | Form: CAPSULE, LIQUID FILLED
Manufacturer: Best Choice  (Valu Merchandisers Company)
Category: otc | Type: HUMAN OTC DRUG LABEL
Date: 20240215

ACTIVE INGREDIENTS: DIMETHICONE 180 mg/1 1
INACTIVE INGREDIENTS: FD&C YELLOW NO. 6; GELATIN; GLYCERIN; FD&C RED NO. 40

Drug Facts

Active ingredient (in each softgel)

Simethicone 180 mg

Purpose

Antigas

Uses

- relieves bloating, pressure, or fullness commonly referred to as gas

Warnings

Stop use and ask a doctor if

condition persists.

If pregnant or breast-feeding,

ask a health professional before use.

Directions

- swallow one or two softgels as needed after meals
- do not exceed two softgels per 24 hours except under the advice and supervision of a physician

Other information

- store between 15-30ºC (59-86ºF)
- protect from heat and moisture

Inactive ingredients

FD&C red #40, FD&C yellow #6, gelatin, glycerin

Questions or comments?

Call 1-877-753-3935 Monday-Friday 9AM-5PM EST

Principal Display Panel

COMPARE TO THE ACTIVE INGREDIENT IN PHAZYME® ULTA STRENGTH†

Ultra Strength

Anti-Gas

Antiflatulent

For Relief of

- Bloating
- pressure
- Discomfort
- Gas

Softgels

†This product is not manufactured or distributed by C.B. Fleet Company Inc., distributor of Phazyme® Ultra Strength

TAMPER EVIDENT: DO NOT USE IF PRINTED SAFETY SEAL UNDER CAP IS BROKEN OR MISSING

KEEP OUTER CARTON FOR COMPLETE WARNINGS AND PRODUCT INFORMATION.

DISTRIBUTED BY:

VALU MERCHANDISERS, CO.

5000 KANSAS AVE

KANSAS CITY, KS 66106

Product Label

BEST CHOICE Ultra Strength Anti-Gas